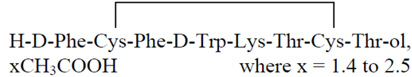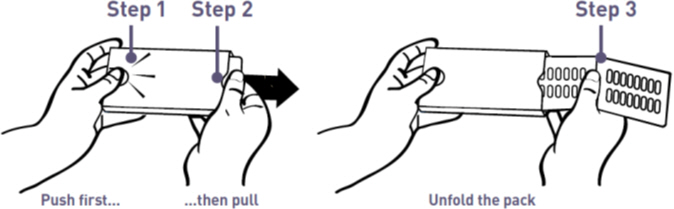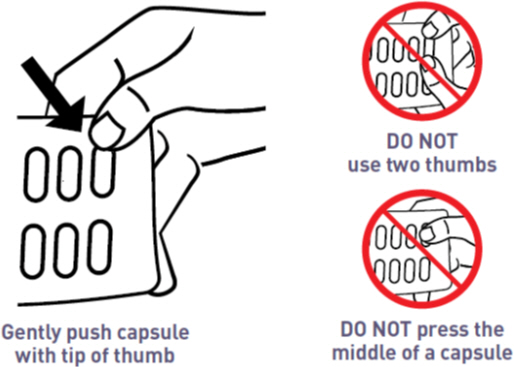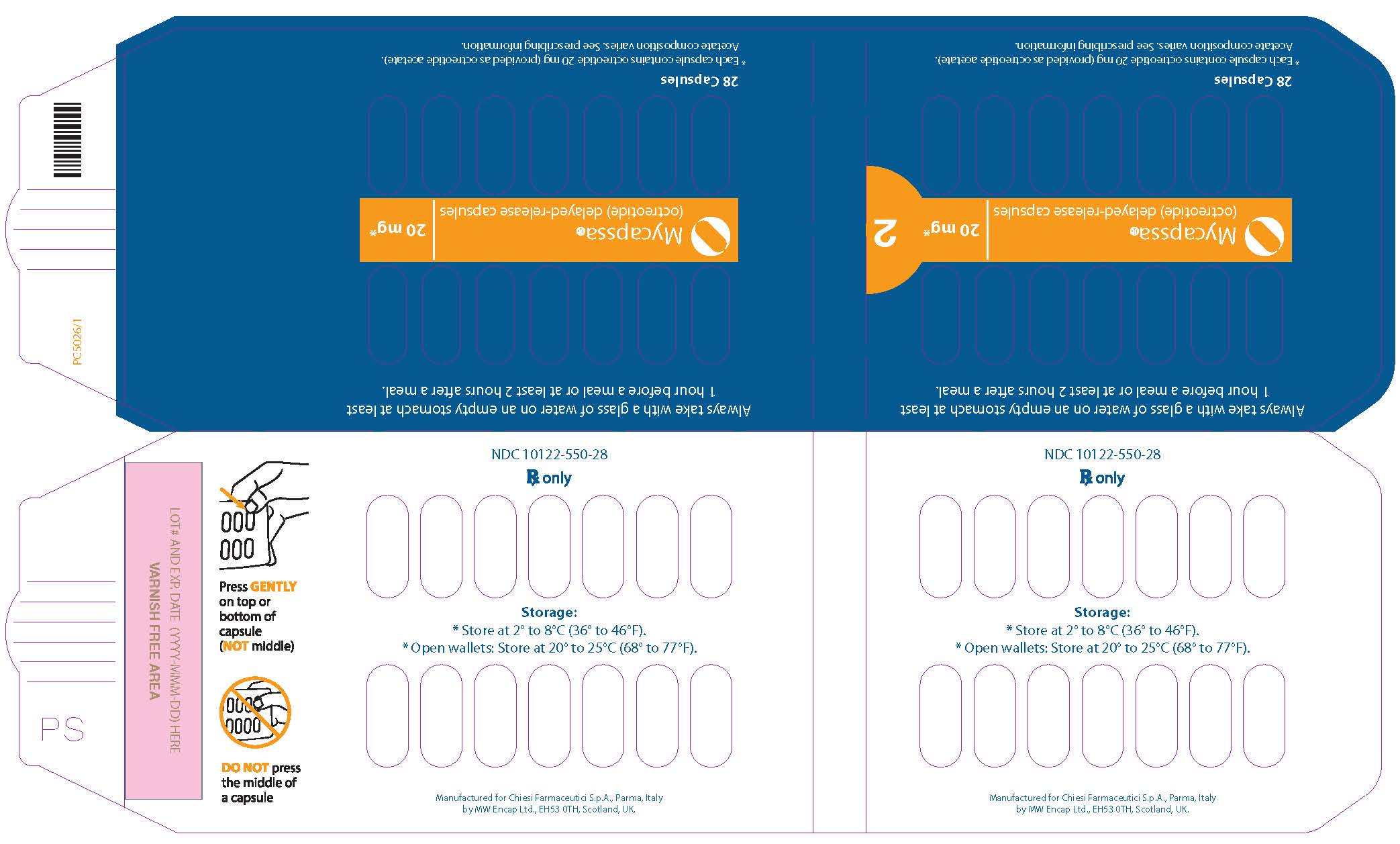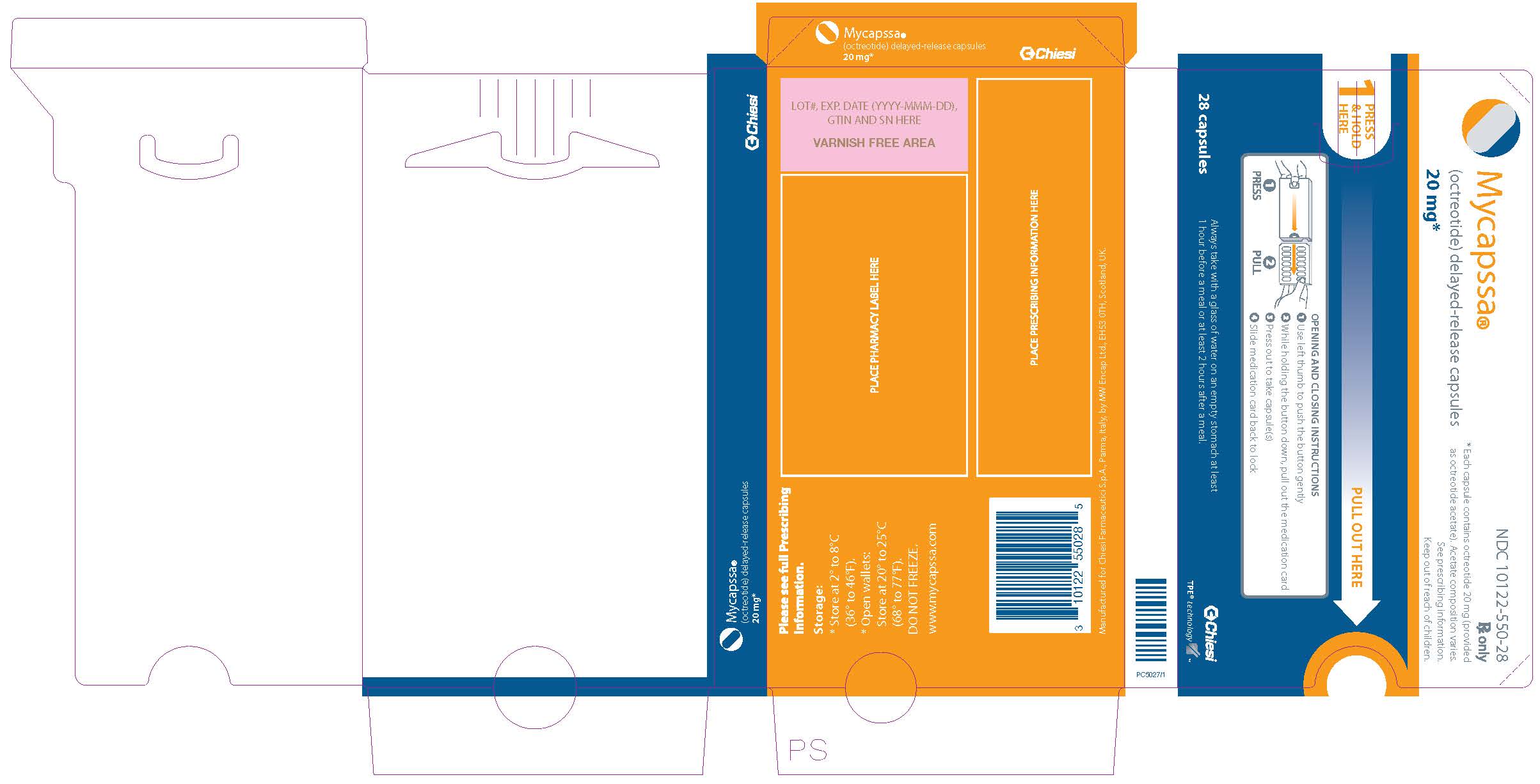 DRUG LABEL: Mycapssa
NDC: 10122-550 | Form: CAPSULE, DELAYED RELEASE
Manufacturer: Chiesi USA, Inc.
Category: prescription | Type: HUMAN PRESCRIPTION DRUG LABEL
Date: 20250724

ACTIVE INGREDIENTS: Octreotide 20 mg/1 1
INACTIVE INGREDIENTS: POVIDONE K12; sodium caprylate; MAGNESIUM CHLORIDE; polysorbate 80; glyceryl monocaprylate; TRICAPRILIN; GELATIN, UNSPECIFIED; METHACRYLIC ACID AND ETHYL ACRYLATE COPOLYMER; TITANIUM DIOXIDE; TRIETHYL CITRATE; SILICON DIOXIDE; SODIUM BICARBONATE; TALC; SODIUM LAURYL SULFATE; SHELLAC; FERROSOFERRIC OXIDE; PROPYLENE GLYCOL; AMMONIA

HIGHLIGHTS OF PRESCRIBING INFORMATION

These highlights do not include all the information needed to use MYCAPSSA® safely and effectively. See full prescribing information for MYCAPSSA.
MYCAPSSA (octreotide) delayed-release capsules, for oral use
Initial U.S. Approval: 1988

RECENT MAJOR CHANGES

Warnings and Precautions, Steatorrhea and Malabsorption of Dietary Fats (5.5) 07/2024

1 INDICATIONS AND USAGE

MYCAPSSA is a somatostatin analog indicated for long-term maintenance treatment in acromegaly patients who have responded to and tolerated treatment with octreotide or lanreotide (‎1).

2 DOSAGE AND ADMINISTRATION

- Take MYCAPSSA orally with a glass of water on an empty stomach, at least 1 hour before a meal or at least 2 hours after a meal (‎2.1).
- Initiate MYCAPSSA at a dosage of 40 mg daily, administered as 20 mg orally twice daily (‎2.2).
- Monitor insulin-like growth factor 1 (IGF-1) levels and patient's signs and symptoms every two weeks during the dose titration or as indicated (‎2.2).
- Titrate the MYCAPSSA dosage, based on IGF-1 levels and patient's signs and symptoms. Increase the dosage in increments of 20 mg (2.2).
- The maximum recommended dosage is 80 mg daily (‎2.2).
- Once the maintenance dosage of MYCAPSSA is achieved, monitor IGF-1 levels and patient's signs and symptoms monthly or as indicated (‎2.2).
- For patients with end-stage renal disease, initiate at a dosage of 20 mg orally once daily. Titrate and adjust the maintenance dosage based on IGF-1 levels, patient's signs and symptoms and tolerability (‎2.4).

3 DOSAGE FORMS AND STRENGTHS

Delayed-release capsules: 20 mg.

4 CONTRAINDICATIONS

Hypersensitivity to octreotide or any of the components of MYCAPSSA.

5 WARNINGS AND PRECAUTIONS

Cholelithiasis and Complications of Cholelithiasis: Monitor periodically. Discontinue if complications of cholelithiasis are suspected (‎5.1).

Hypoglycemia or Hyperglycemia: Monitor glucose and adjust antidiabetic treatment as needed (‎5.2).

Thyroid Function Abnormalities: Hypothyroidism may occur. Assess thyroid function periodically (5.3).

Cardiac Function: Bradycardia, arrhythmia, or conduction abnormalities may occur. Drugs that have bradycardia effects may need dosage adjustments (5.4, ‎7.2).

Steatorrhea and Malabsorption of Dietary Fats: New onset steatorrhea, stool discoloration, loose stools, abdominal bloating, and weight loss may occur. If new occurrence or worsening of these symptoms are reported, evaluate for potential pancreatic exocrine insufficiency (5.5)

Change in vitamin B12 levels: Monitor vitamin B12 levels during treatment (5.6).

6 ADVERSE REACTIONS

Most common adverse reactions (incidence >10 %) are nausea, diarrhea, headache, arthralgia, asthenia, hyperhidrosis, peripheral swelling, blood glucose increased, vomiting, abdominal discomfort, dyspepsia, sinusitis, osteoarthritis (‎6.1).

To report SUSPECTED ADVERSE REACTIONS, contact Chiesi Farmaceutici S.p.A. at 1-888-661-9260 or FDA at 1-800-FDA-1088 or www.fda.gov/medwatch

7 DRUG INTERACTIONS

- Proton Pump Inhibitors, H2-receptor Antagonists, or Antacids: may decrease bioavailability of MYCAPSSA and the MYCAPSSA dose may need to be increased (‎7).
- Cyclosporine: may have decreased bioavailability and require dose adjustment (7).
- Insulin and Antidiabetic Drugs: patients receiving insulin or antidiabetic drugs agents may require dose adjustment (‎7).
- Digoxin: exposure may be decreased and assessment of clinical response to digoxin should be performed (‎7).
- Lisinopril: bioavailability may be increased, monitor patient's blood pressure and adjust dose of lisinopril if needed (‎7).
- Levonorgestrel: counsel women to use an alternative non-hormonal method of contraception or a back-up method when MYCAPSSA is used with combined oral contraceptives (‎7).
- Bromocriptine: dose adjustment of bromocriptine may be necessary (‎7).
- Beta Blocker and Calcium Channel Blockers: dose adjustment of beta blockers or calcium channel blockers may be necessary (‎7).
- Drugs Metabolized by CYP 450 Enzymes: concomitant use with other drugs mainly metabolized by CYP3A4 that have a narrow therapeutic index (e.g., quinidine) should be used with caution and increased monitoring may be required (‎7).

8 USE IN SPECIFIC POPULATIONS

Females and Males of Reproductive Potential: Advise premenopausal females of the potential for an unintended pregnancy (‎8.3).

FULL PRESCRIBING INFORMATION

1 INDICATIONS AND USAGE

MYCAPSSA is indicated for long-term maintenance treatment in acromegaly patients who have responded to and tolerated treatment with octreotide or lanreotide.

2 DOSAGE AND ADMINISTRATION

2.1 Important Administration Instructions

- Take MYCAPSSA orally with a glass of water on an empty stomach, at least 1 hour before a meal or at least 2 hours after a meal.
- Swallow MYCAPSSA capsules whole. Do not crush or chew the capsules.

2.2 Recommended Dosage, Titration, and Monitoring

- Initiate MYCAPSSA at a dosage of 40 mg daily, administered as 20 mg orally twice daily.
- Monitor insulin-like growth factor 1 (IGF-1) levels and patient's signs and symptoms every two weeks during the dose titration or as indicated.
- Titrate the MYCAPSSA dosage based on IGF-1 levels and patient's signs and symptoms. Increase the dosage in increments of 20 mg daily.
- For MYCAPSSA dosages of 60 mg daily, administer as 40 mg in the morning and 20 mg in the evening.
- For MYCAPSSA dosages of 80 mg daily, administer as 40 mg twice daily.
- The maximum recommended dosage of MYCAPSSA is 80 mg daily.
- Once the maintenance dosage of MYCAPSSA is achieved, monitor IGF-1 levels and patient's signs and symptoms monthly or as indicated.

2.3 Dosage Interruptions and Modifications

- If IGF-1 levels remain above the upper normal limit after treatment with the maximum recommended dosage of 80 mg daily or the patient cannot tolerate treatment with MYCAPSSA, consider discontinuing MYCAPSSA and switching patient to another somatostatin analog.
- Withdraw MYCAPSSA therapy periodically to assess disease activity. If IGF-1 levels increase and signs and symptoms recur, resume MYCAPSSA therapy.

2.4 Recommended Dosage in Patients with End Stage Renal Disease

For patients with end-stage renal disease, initiate MYCAPSSA at a dosage of 20 mg orally once daily. Titrate and adjust the maintenance dosage of MYCAPSSA based on IGF-1 levels, patient's signs and symptoms and tolerability [see Dosage and Administration (‎2.2, ‎2.3), Use in Specific Populations (‎8.6)].

2.5 Dosage Modifications with Concomitant Use of Proton Pump Inhibitors, H2-receptor Antagonists, or Antacids

Patients taking proton pump inhibitors, H2-receptor antagonists, or antacids concomitantly with MYCAPSSA may require increased dosages of MYCAPSSA [see Drug Interactions (‎7.1)].

3 DOSAGE FORMS AND STRENGTHS

Delayed-release capsules: 20 mg. White hard gelatin capsules imprinted with "OT" on one half of the capsule and "20" on the other half. Each capsule contains 20 mg octreotide, provided as octreotide acetate.

4 CONTRAINDICATIONS

Hypersensitivity to octreotide or any of the components of MYCAPSSA. Anaphylactoid reactions, including anaphylactic shock, have been reported in patients receiving octreotide [see Adverse Reactions (‎6.3)].

5 WARNINGS AND PRECAUTIONS

5.1 Cholelithiasis and Complications of Cholelithiasis

MYCAPSSA may inhibit gallbladder contractility and decrease bile secretion, which may lead to gallbladder abnormalities or sludge. Gallbladder-related adverse reactions have been reported in clinical trials in patients receiving MYCAPSSA. There have been postmarketing reports of cholelithiasis (gallstones) in patients taking somatostatin analogs resulting in complications, including cholecystitis, cholangitis, pancreatitis and requiring cholecystectomy [see Adverse Reactions (‎6)]. Monitor patients periodically. If complications of cholelithiasis are suspected, discontinue MYCAPSSA and treat appropriately.

5.2 Hyperglycemia and Hypoglycemia

MYCAPSSA alters the balance between the counter-regulatory hormones, insulin, glucagon, and growth hormone, which may result in hypoglycemia, or hyperglycemia, or diabetes mellitus. In clinical trials with MYCAPSSA, the following adverse reactions were reported: increased blood glucose (7%), hypoglycemia (4%), and diabetes mellitus (1%) [see Adverse Reactions (‎6.1)]. Blood glucose levels should be monitored when MYCAPSSA treatment is initiated, or when the dose is altered. Adjust antidiabetic treatment accordingly.

5.3 Thyroid Function Abnormalities

MYCAPSSA suppresses the secretion of thyroid-stimulating hormone, which may result in hypothyroidism. In clinical trials with MYCAPSSA, the following adverse reactions were reported: hypothyroidism (1%), increased TSH (1%), or decreased free T4 (1%) [see Adverse Reactions (‎6.1)]. Assess thyroid function periodically during treatment with MYCAPSSA.

5.4 Cardiac Function Abnormalities

Cardiac conduction abnormalities and other ECG changes including QT prolongation, axis shifts, early repolarization, low voltage, R/S transition, and early R wave progression, have occurred during treatment with octreotide. In MYCAPSSA clinical trials the following adverse reactions were reported: bradycardia (2%), conduction abnormalities (1%), and arrhythmias/tachycardia (2%) [see Adverse Reactions (‎6)]. These ECG changes may occur in patients with acromegaly. Dosage adjustments of concomitantly used drugs that have bradycardia effects (i.e. beta-blockers) may be necessary [see Drug Interactions (‎7.2)].

5.5 Steatorrhea and Malabsorption of Dietary Fats

New onset steatorrhea, stool discoloration and loose stools have been reported in patients receiving somatostatin analogs, including octreotide. Somatostatin analogs reversibly inhibit secretion of pancreatic enzymes and bile acids, which may result in malabsorption of dietary fats and subsequent symptoms of steatorrhea, loose stools, abdominal bloating, and weight loss. If new occurrence or worsening of these symptoms are reported in patients receiving MYCAPSSA, evaluate patients for potential pancreatic exocrine insufficiency and manage accordingly.

5.6 Changes in Vitamin B12 Levels

Decreased vitamin B12 levels and abnormal Schilling’s tests have been observed in some patients receiving octreotide. Monitor vitamin B12 levels during treatment with MYCAPSSA.

6 ADVERSE REACTIONS

The following important adverse reactions are described below and elsewhere in the labeling:

- Cholelithiasis and Complications of Cholelithiasis [see Warnings and Precautions (‎5.1)]
- Hyperglycemia and Hypoglycemia [see Warnings and Precautions (‎5.2)]
- Thyroid Function Abnormalities [see Warnings and Precautions (‎5.3)]
- Cardiac Function Abnormalities [see Warnings and Precautions (‎5.4)]
- Steatorrhea and Malabsorption of Dieatary Fats [see Warnings and Precautions (‎5.5)]
- Changes in Vitamin B12 Levels [see Warnings and Precautions (5.6)]

6.1 Clinical Studies Experience

Because clinical trials are conducted under widely varying conditions, adverse reaction rates observed in the clinical trials of a drug cannot be directly compared to rates in the clinical trials of another drug and may not reflect the rates observed in practice.

MYCAPSSA has been evaluated in patients with acromegaly in a placebo-controlled study [see Clinical Studies (‎14)] and an open-label baseline-controlled study. The data reflect exposure of 183 patients to MYCAPSSA for a mean duration of 29 weeks. In the overall study population, 56% were female and the average age of patients was 54.3 years. Adverse reactions occurring ≥ 5% and greater than placebo for the placebo-controlled study are presented in Table 1 and adverse reactions occurring ≥ 5% in the open-label study are presented in Table 2.

Table 1: Adverse Reactions Occurring ≥ 5% and Greater than Placebo in a Placebo-Controlled Study with MYCAPSSA in Acromegaly Patients
 | MYCAPSSA % (N=28) | PLACEBO % (N=28)
Diarrhea | 29 | 21
Nausea | 21 | 11
Blood glucose increased [Includes blood glucose increased, hyperglycemia and glycosylated hemoglobin increased] | 14 | 7
Vomiting | 14 | 0
Abdominal discomfort | 14 | 11
Dyspepsia | 11 | 4
Sinusitis | 11 | 0
Osteoarthritis | 11 | 0
Urinary tract infection | 7 | 4
Pain | 7 | 0
Large intestine polyp | 7 | 0
Cholelithiasis | 7 | 4

Table 2: Adverse Reactions Occurring ≥ 5% in an Open-Label Study with MYCAPSSA in Acromegaly Patients
 | MYCAPSSA % (N=155)
Headache | 33
Nausea | 30
Arthralgia | 26
Asthenia | 22
Hyperhidrosis | 21
Diarrhea | 18
Peripheral swelling | 16
Dyspepsia | 8
Abdominal pain upper | 8
Abdominal distension | 7
Nasopharyngitis | 7
Influenza | 7
Blood glucose increased [Includes blood glucose increased, hyperglycemia and impaired fasting glucose] | 6
Vomiting | 6
Flatulence | 6
Back pain | 6
Abdominal pain | 5
Dizziness | 5
Fatigue | 5
Upper respiratory tract infection | 5
Hypertension | 5

Other Adverse Reactions

Gallbladder Abnormalities

In the placebo-controlled study, in patients treated with MYCAPSSA, acute cholecystitis occurred in 4% of patients.

In the open-label study, cholelithiasis occurred in 4.5% of patients and bile duct obstruction, bile duct stone, acute cholecystitis and jaundice occurred in 1% of patients each.

Hypoglycemia/Hyperglycemia

In the placebo-controlled study, 18% of patients treated with MYCAPSSA and 4% of patients treated with placebo developed at least one glucose value above the upper normal limit. All patients with abnormal glucose values were asymptomatic. Asymptomatic hypoglycemia was reported in 4% of patients.

In the open-label study 16% of patients developed a glucose value above the upper limit of normal. Asymptomatic hypoglycemia was reported in 4% and symptomatic hypoglycemia was reported in 1% of patients. Diabetes was reported in 1% of patients.

Hypothyroidism

In the open-label study, hypothyroidism, increased TSH, or decreased free T4 were reported in 1% of patients.

Cardiac

In the open-label study, bradycardia was reported in 2%, conduction abnormalities in 1%, and arrhythmias/tachycardia in 2% of patients.

Gastrointestinal

Gastrointestinal symptoms were the most commonly reported adverse reactions with MYCAPSSA.

In the placebo-controlled study, gastrointestinal adverse reactions were reported in 68% of patients treated with MYCAPSSA. These adverse reactions were diarrhea, nausea, vomiting, abdominal discomfort, dyspepsia, large intestinal polyp, abdominal pain, constipation, and flatulence. The adverse reactions were mild to moderate, occurred mostly during the initial 3 months of treatment, and resolved on treatment within a median duration of 8 days.

In the open-label study, gastrointestinal adverse reactions were reported in 57% of patients. Gastrointestinal adverse reactions occurring in ≥ 1% of patients were nausea, diarrhea, dyspepsia, abdominal pain, abdominal distention, vomiting, flatulence, constipation, gastroesophageal reflux disease, abdominal discomfort, frequent bowel movement, gastritis, hemorrhoids, dry mouth, and gastrointestinal motility disorder. Large intestinal polyp was reported in 1 patient. The adverse reactions were mostly mild to moderate, occurred during the initial 2 months of treatment, and resolved on treatment within a median of 13 days. Ten patients discontinued treatment due to gastrointestinal adverse reactions.

6.2 Immunogenicity

As with all therapeutic peptides, there is potential for immunogenicity. The detection of antibody formation is highly dependent on the sensitivity and specificity of the assay. Additionally, the observed incidence of antibody (including neutralizing antibody) positivity in an assay may be influenced by several factors including assay methodology, sample handling, timing of sample collection, concomitant medications, and underlying disease. For these reasons, comparison of the incidence of antibodies in the studies described below with the incidence of antibodies in other studies or to other octreotide acetate products may be misleading.

No antibodies to the octreotide peptide from MYCAPSSA were detected in 149 patients assessed in the open label study throughout 13 months of treatment.

6.3 Postmarketing Experience

The following adverse reactions have been identified during the post-approval use of octreotide acetate. Because these reactions are reported voluntarily from a population of uncertain size, it is not always possible to reliably estimate their frequency or establish a causal relationship to drug exposure.

- Blood and lymphatic: pancytopenia, thrombocytopenia
- Cardiac: myocardial infarction, cardiac arrest, atrial fibrillation
- Ear and labyrinth: deafness
- Endocrine: diabetes insipidus, adrenal insufficiency in patients 18 months of age and under, pituitary apoplexy
- Eye: glaucoma, visual field defect, scotoma, retinal vein thrombosis
- Gastrointestinal: intestinal obstruction, peptic/gastric ulcer, abdomen enlarged
- General and administration site: generalized edema, facial edema
- Hepatobiliary: gallbladder polyp, fatty liver, hepatitis
- Immune: anaphylactoid reactions including anaphylactic shock
- Infections and infestations: appendicitis
- Laboratory abnormalities: increased liver enzymes, CK increased, creatinine increased
- Metabolism and nutrition: diabetes mellitus
- Musculoskeletal: arthritis, joint effusion, Raynaud's syndrome
- Nervous System: convulsions, aneurysm, intracranial hemorrhage, hemiparesis, paresis, suicide attempt, paranoia, migraines, Bell's palsy, aphasia
- Renal and urinary: renal failure, renal insufficiency
- Reproductive and breast: gynecomastia, galactorrhea, libido decrease, breast carcinoma
- Respiratory: status asthmaticus, pulmonary hypertension, pulmonary nodule, pneumothorax aggravated
- Skin and subcutaneous tissue: urticaria, cellulitis, petechiae
- Vascular: orthostatic hypotension, hematuria, gastrointestinal hemorrhage, arterial thrombosis of the arm

7 DRUG INTERACTIONS

7.1 Effects of Other Drugs on MYCAPSSA

Proton Pump Inhibitors, H2-receptor Antagonists, or Antacids
Clinical Impact: | Concomitant administration of MYCAPSSA with esomeprazole resulted in a decrease in the bioavailability for MYCAPSSA [See Clinical Pharmacology (‎12.3)]. Drugs that alter the pH of the upper GI tract (e.g., other proton pump inhibitors (PPIs), H2-receptor antagonists, and antacids) may alter the absorption of MYCAPSSA and lead to a reduction in bioavailability.
Intervention: | Co-administration of MYCAPSSA with PPIs, H2-blockers, or antacids may require increased doses of MYCAPSSA.

7.2 Effects of MYCAPSSA on Other Drugs

Cyclosporine
Clinical Impact: | Concomitant administration of MYCAPSSA with cyclosporine resulted in a decrease in cyclosporine bioavailability [see Clinical Pharmacology (‎12.3)].
Intervention: | Adjustment of cyclosporine dose to maintain therapeutic levels may be necessitated.
Insulin and Antidiabetic Drugs
Clinical Impact: | MYCAPSSA inhibits the secretion of insulin and glucagon.
Intervention: | Monitor blood glucose levels in diabetic patients upon MYCAPSSA initiation and subsequent dose adjustment. Patients receiving insulin or antidiabetic drugs agents may require dose adjustment of these therapeutic agents.
Digoxin
Clinical Impact: | Concomitant administration of MYCAPSSA with digoxin resulted in a decrease in digoxin peak exposure [see Clinical Pharmacology (‎12.3)].
Intervention: | Digoxin has a narrow therapeutic ratio and careful assessment of clinical response should be performed when digoxin is concomitantly administered with MYCAPSSA.
Lisinopril
Clinical Impact: | Concomitant administration of MYCAPSSA increases lisinopril bioavailability [see Clinical Pharmacology (‎12.3)].
Intervention: | Monitor patient's blood pressure and adjust the dosage of lisinopril if needed.
Levonorgestrel
Clinical Impact: | Concomitant administration of MYCAPSSA with levonorgestrel decreases levonorgestrel bioavailability [see Clinical Pharmacology (‎12.3)].
Intervention: | Decreased bioavailability may potentially diminish the effectiveness of combined oral contraceptives (COCs) or increase breakthrough bleeding. Counsel women to use an alternative non-hormonal method of contraception or a back-up method when MYCAPSSA is used with COCs.
Bromocriptine
Clinical Impact: | Concomitant administration of MYCAPSSA with bromocriptine may increase the systemic exposure of bromocriptine [see Clinical Pharmacology (‎12.3)].
Intervention: | Dose adjustment of bromocriptine may be necessary.
Beta Blocker and Calcium Channel Blockers
Clinical Impact: | MYCAPSSA may cause bradycardia in acromegaly patients.
Intervention: | Patients receiving beta blockers or calcium channel blockers may require dose adjustments of these therapeutic agents.
Drugs Metabolized by CYP 450 Enzymes
Clinical Impact: | Limited published data indicate that somatostatin analogs including MYCAPSSA may decrease the metabolic clearance of compounds known to be metabolized by cytochrome P450 enzymes, which may be due to the suppression of GH.
Intervention: | Concomitant use with other drugs mainly metabolized by CYP3A4 that have a narrow therapeutic index (e.g., quinidine) should be used with caution and increased monitoring may be required.

8 USE IN SPECIFIC POPULATIONS

8.1 Pregnancy

Risk Summary

Available data from case reports with octreotide acetate use in pregnant women are insufficient to identify a drug-associated risk of major birth defects, miscarriage or adverse maternal or fetal outcomes. Animal reproduction studies have not been conducted with MYCAPSSA. No adverse developmental effects were observed with intravenous administration of octreotide to pregnant rats and rabbits during organogenesis at doses 7 and 13 times, respectively, the clinical dose based on octreotide injection body surface area. Transient growth retardation, with no impact on postnatal development, was observed in rat offspring from a pre- and post-natal study of octreotide at intravenous doses below the clinical dose based on octreotide injection body surface area (see Data).

The estimated background risk of major birth defects and miscarriage for the indicated population is unknown. In the U.S. general population, the estimated background risk of major birth defects and miscarriage in clinically recognized pregnancies is 2%-4% and 15%-20%, respectively.

Data

Animal Data

In embryo-fetal development studies in rats and rabbits, pregnant animals received intravenous doses of octreotide up to 1 mg/kg/day during the period of organogenesis. A slight reduction in body weight gain was noted in pregnant rats at 0.1 and 1 mg/kg/day. There were no maternal effects in rabbits or embryo-fetal effects in either species up to the maximum dose tested. At 1 mg/kg/day in rats and rabbits, the dose multiple was approximately 7 and 13 times, respectively, the clinical dose based on octreotide injection body surface area.

In a pre- and post-natal development rat study at intravenous doses of 0.02-1 mg/kg/day, a transient growth retardation of the offspring was observed at all doses which was possibly a consequence of growth hormone inhibition by octreotide. The doses attributed to the delayed growth are below the clinical dose based on octreotide injection body surface area.

8.2 Lactation

Risk Summary

There is no information available on the presence of octreotide in human milk, the effects of the drug on the breastfed infant, or the effects of the drug on milk production. Studies show that octreotide administered subcutaneously passes into the milk of lactating rats (see Data). When a drug is present in animal milk, it is likely that the drug will be present in human milk. The developmental and health benefits of breastfeeding should be considered along with the mother's clinical need for MYCAPSSA and any potential adverse effects on the breastfed child from MYCAPSSA or from the underlying maternal condition.

Data

Following a subcutaneous dose (1 mg/kg) of octreotide to lactating rats, transfer of octreotide into milk was observed at a low concentration compared to plasma (milk/plasma ratio of 0.009).

8.3 Females and Males of Reproductive Potential

Discuss the potential for unintended pregnancy with premenopausal women as the therapeutic benefits of a reduction in GH levels and normalization of IGF-1 concentration in acromegalic females treated with octreotide may lead to improved fertility.

8.4 Pediatric Use

Safety and efficacy of MYCAPSSA in pediatric patients have not been established.

In post-marketing reports, serious adverse reactions, including hypoxia, necrotizing enterocolitis, and death, have been reported with octreotide injection use in pediatric patients, most notably in children under 2 years of age.

8.5 Geriatric Use

Clinical studies of octreotide did not include sufficient numbers of subjects aged 65 and over to determine whether they respond differently from younger subjects. In MYCAPSSA clinical studies, 39 patients (21%) were age 65 years or over and 1 patient was age 75 years or over. No overall differences in safety or effectiveness were observed between these patients and younger patients, and other reported clinical experience has not identified differences in responses between the elderly and younger patients, but greater sensitivity of some older individuals cannot be ruled out.

8.6 Renal Impairment

In patients with mild, moderate, or severe renal impairment there is no dose adjustment recommended for MYCAPSSA. There is a significant increase in octreotide exposure in patients with end stage renal disease (ESRD). Start patients with ESRD on MYCAPSSA 20 mg orally daily. Adjust the maintenance dose thereafter based on IGF-1 levels, patient's signs and symptoms, and tolerability [see Dosage and Administration (‎2.3) and Clinical Pharmacology (‎12.3)].

8.7 Hepatic Impairment

Patients with liver cirrhosis and patients with fatty liver disease showed prolonged elimination of octreotide following subcutaneous administration of drug [see Clinical Pharmacology (‎12.3)].

10 OVERDOSAGE

A limited number of accidental overdoses of injectable octreotide acetate in adults has been reported. The doses ranged from 2.4 mg/day to 6 mg/day administered by continuous infusion or subcutaneously 1.5 mg three times a day. Adverse reactions in some patients included arrhythmia, hypotension, cardiac arrest, brain hypoxia, pancreatitis, hepatic steatosis, hepatomegaly, lactic acidosis, flushing, diarrhea, lethargy, weakness, and weight loss.

If overdose occurs, contact Poison Control (1-800-222-1222) for latest recommendations.

11 DESCRIPTION

MYCAPSSA delayed release capsules contain octreotide acetate, a somatostatin analog. Octreotide is known chemically as L-cysteinamide, D-phenylalanyl-L-cysteinyl-L-phenylalanyl-D-tryptophyl-L-lysyl-L-threonyl-N-[2-hydroxy-1-(hydroxy-methyl) propyl]-, cyclic (2→7)-disulfide; [R-(R*,R*)].

The molecular weight of octreotide is 1019.3 (free peptide, C49H66N10O10S2) and its amino acid sequence is:

MYCAPSSA (octreotide) delayed-release capsules are enteric-coated capsules for oral use. Each capsule contains 20 mg of octreotide (provided as octreotide acetate). Octreotide is present as a salt with 1.4 to 2.5 molar equivalents of acetate. The capsules contain the following inactive ingredients: polyvinylpyrrolidone (PVP-12), sodium caprylate, magnesium chloride, polysorbate 80, glyceryl monocaprylate, glyceryl tricaprylate, gelatin, gelatin capsules, and Acryl-EZE® (methacrylate). The capsule is printed with "OT 20" in Opacode® black ink.

12 CLINICAL PHARMACOLOGY

12.1 Mechanism of Action

Octreotide exerts pharmacologic actions similar to the natural hormone somatostatin, but is a more potent inhibitor of GH, glucagon, and insulin than somatostatin. Like somatostatin, it also suppresses luteinizing hormone (LH) response to gonadotropin-releasing hormone (GnRH), decreases splanchnic blood flow, and inhibits release of serotonin, gastrin, vasoactive intestinal peptide, secretin, motilin, and pancreatic polypeptide.

12.2 Pharmacodynamics

In a single-dose PK study conducted in healthy volunteers, inhibition of GH (as measured by Cavg) was observed in all subjects receiving MYCAPSSA, as compared to their GH levels prior to MYCAPSSA.

In a study designed to assess the duration of MYCAPSSA-induced increased intestinal permeability, an increase in paracellular permeability was observed 2 hours after MYCAPSSA administration and returned to baseline by 5.5 hours after MYCAPSSA administration. MYCAPSSA-induced permeability is completely reversible within this timeframe.

MYCAPSSA maintained GH and IGF-1 levels in patients with acromegaly.

Single doses of octreotide acetate given subcutaneously have been shown to inhibit gallbladder contractility and to decrease bile secretion in normal volunteers. In clinical trials the incidence of gallstone or biliary sludge formation was markedly increased [see Warnings and Precautions (‎5.1)].

Octreotide acetate may cause clinically significant suppression of TSH [see Warnings and Precautions (‎5.3)].

12.3 Pharmacokinetics

Absorption

In healthy subjects, similar systemic exposure (AUC) was observed between a single dose oral administration of MYCAPSSA (20 mg octreotide acetate), and a single dose of subcutaneous Sandostatin IR (0.1 mg octreotide acetate). Peak octreotide levels (Cmax) were 33% lower following oral administration compared to the subcutaneous route. Absorption time was longer following oral administration compared to the subcutaneous route; peak concentrations were reached at a median of 1.67–2.5 hours after 20 mg MYCAPSSA administration compared to 0.5 hours for the subcutaneous administration.

In healthy subjects, after single-dose oral administration of MYCAPSSA, the systemic exposure of octreotide (Cmax, AUC0-24, and AUC0-inf) increased dose-proportionally at doses ranging from 3–40 mg.

In patients with acromegaly, there was a dose-related increase in the mean plasma octreotide concentrations after chronic administration of MYCAPSSA 40 mg (20 mg bid), 60 mg (40 mg AM / 20 mg PM), and 80 mg (40 mg AM / 40 mg PM) bid. Mean peak concentrations (Cmax) following chronic dosing were lower in patients with acromegaly (mean [CV%] = 2.51 ng/mL [80%] and 5.30 ng/mL [76%] at 20 and 40 mg bid, respectively) compared to single-dose peak concentrations observed in healthy subjects at the same dose (mean [CV%] = 3.62 [53%] and 8.21 ng/mL [88%] at 20 and 40 mg, respectively).

Effect of Food on Oral Absorption

In healthy subjects, data from a single-dose, crossover PK study of food effect demonstrated that administration of MYCAPSSA 20 mg capsules with food led to an approximate 90% decrease in the rate (Cmax) and extent of absorption (AUC0-t).

Distribution

In healthy volunteers, the distribution half-life (tα½) of octreotide acetate from plasma after subcutaneous administration was 0.2 h, the volume of distribution (Vdss) was estimated to be 13.6 L, and the total body clearance ranged from 7–10 L/hr. In blood, the distribution into the erythrocytes was found to be negligible and about 65% was bound in the plasma in a concentration-independent manner. Binding was mainly to lipoprotein and, to a lesser extent, to albumin.

In patients with acromegaly, the Vdss following subcutaneous administration was increased compared to healthy volunteers, estimated to be 21.6 L; mean peak concentrations were lower in acromegaly patients compared to healthy volunteers (2.8 ng/mL vs 5.2 ng/mL, respectively after 0.1 ng/mL dose).

Elimination

According to data obtained with the immediate-release octreotide subcutaneous injection, approximately 32% of the dose is excreted unchanged in the urine.

In healthy subjects, there was no effect of route of administration on octreotide elimination, and comparable mean elimination half-lives (t½) of 2.3 hours and 2.7 hours were demonstrated between subcutaneous injection and oral octreotide treatments, respectively.

In patients with acromegaly, elimination after chronic dosing was slightly slower than that seen in healthy volunteers, with mean apparent half-life values at steady state ranging from 3.2–4.5 hours across doses (20 mg, 40 mg, 60 mg, and 80 mg). Elimination is complete approximately 48 hours after the last dose in patients who have achieved steady-state plasma levels. Minimal accumulation (approximately 10%) was observed in patients after repeat administration of MYCAPSSA.

Specific Populations

Geriatric Patients

In patients 65 years of age and older, after subcutaneous administration of octreotide acetate, the half-life of octreotide increased significantly (46%) and clearance of octreotide decreased significantly (26%).

Patients with Renal Impairment

Exposure in patients with severe renal impairment was not substantially different from that of the matched controls. Following oral administration of a single dose of 20 mg MYCAPSSA to patients with severe renal impairment (eGFR 15–29 mL/min/1.73m^2) and patients with end-stage renal disease (ESRD) requiring dialysis, patients with ESRD on dialysis had a 46% decrease in clearance with a corresponding 87% increase in AUC and 85% increase in t½ compared to matched healthy subjects. ESRD patients had higher mean plasma concentrations than did those with severe renal impairment with higher mean values for Cmax (9.30 ng/mL compared to 6.13 ng/mL in the matched controls), AUC0–t (68.0 h∙ng/mL compared to 32.2 h∙ng/mL in the matched controls), AUCinf (69.5 h∙ng/mL compared to 32.4 h∙ng/mL in the matched controls), and t½ (7.09 hr compared to 3.84 hr in the matched controls), consistent with the known effect of renal impairment on octreotide exposure [see Use in Specific Populations (‎8.6)].

Patients with Hepatic Impairment

In patients with liver cirrhosis, after subcutaneous administration of octreotide acetate, prolonged elimination of drug was observed, with octreotide acetate t½ increasing from 1.9–3.7 hr and total body clearance decreasing from 7–10 L/hr to 5.9 L/hr, whereas patients with fatty liver disease showed t½ increased to 3.4 hr and total body clearance of 8.2 L/hr.

Drug Interactions

Limited published data indicate that somatostatin analogs including MYCAPSSA may decrease the metabolic clearance of compounds known to be metabolized by cytochrome P450 enzymes, which may be due to the suppression of GH [see Drug Interactions (‎7.2)].

Octreotide has been associated with alterations in nutrient absorption, so it may have an effect on absorption of orally administered drugs.

Table 3 Effect of Co-administered Drugs on MYCAPSSA Systemic Exposure
Co-administered drug and dosing regimen | MYCAPSSA
Co-administered drug and dosing regimen | Dose (mg) | Mean Ratio (ratio with/without co-administered drug) No Effect=1.0
Co-administered drug and dosing regimen | Dose (mg) | Change in AUC | Change in Cmax
Esomeprazole 40 mg QD on days 2-7 | 20 mg on Day 1 and 20 mg on Day 7 | 0.59^1 (0.40 – 0.88)^2 | 0.55^1 (0.40 – 0.75)^2
Metoclopramide 20 mg | 40 mg | 0.91 (0.61 – 1.35) | 0.95 (0.62 – 1.44)
Loperamide 4 mg | 40 mg | 0.97 (0.65 – 1.44)^2 | 0.91 (0.59 – 1.39)^2
^1Clinically significant [see Dosage and Administration (‎2) and Drug Interactions (‎7.1, ‎7.2)]
^2Mean ratio with 90% CI (with/without co-administered drug, e.g., 1= no change, 0.6 = 40% decrease,1.3=1.3-fold increase in exposure)

Table 4 Effect of MYCAPSSA on Systemic Exposure of Co-administered Drugs
Co-administered drug and dosing regimen | MYCAPSSA
Co-administered drug and dosing regimen | Dose (mg)^1 | Mean Ratio (ratio with/without co-administered drug) No Effect=1.0
Co-administered drug and dosing regimen | Dose (mg)^1 | Change in AUC | Change in Cmax
Cyclosporine 300 mg | 20 mg | 0.38^2 (0.31 – 0.46)^3 | 0.29^2 (0.22 – 0.37)^3
Digoxin 0.5 mg | 40 mg | 1.0 (0.94 – 1.13)^3 | 0.63^2 (0.55 – 0.72)^3
Lisinopril 20 mg | 40 mg | 1.40^2 (1.21 – 1.61)^3 | 1.50^2 (1.32 – 1.71)^3
Ethinyl Estradiol 0.06 mg | 40 mg | 0.94 (0.86 – 1.03)^3 | 0.92 (0.83 – 1.01)^3
Levonorgestrel 0.3 mg | 40 mg | 0.76^2 (0.67 – 0.86)^3 | 0.62^2 (0.54 – 0.71)^3
^1Single dose
^2Clinically significant [see Dosage and Administration (‎2) and Drug Interactions (‎7.1, ‎7.2)]
^3Mean ratio with 90% CI (with/without co-administered drug, e.g., 1= no change, 0.6 = 40% decrease, 1.5=1.5-fold increase in exposure)

13 NONCLINICAL TOXICOLOGY

13.1 Carcinogenesis, Mutagenesis, Impairment of Fertility

Studies in laboratory animals have demonstrated no mutagenic potential of octreotide acetate.

No carcinogenicity studies have been conducted with MYCAPSSA. No carcinogenic potential was demonstrated in mice treated subcutaneously with octreotide acetate for 85–99 weeks at doses up to 2000 mcg/kg/day (8 times the clinical dose based on octreotide injection body surface area). In a 116-week subcutaneous study in rats administered octreotide acetate, a 27% and 12% incidence of injection-site sarcomas or squamous cell carcinomas was observed in males and females, respectively, at the highest dose level of 1250 mcg/kg/day (10 times the clinical dose based on octreotide injection body surface area) compared to an incidence of 8% to 10% in the vehicle-control groups. The increased incidence of injection-site tumors was most probably caused by irritation and the high sensitivity of the rat to repeated subcutaneous injections at the same site. There was also a 15% incidence of uterine adenocarcinomas in the 1250 mcg/kg/day females compared to 7% in the saline-control females and 0% in the vehicle-control females. The presence of endometritis coupled with the absence of corpora lutea, the reduction in mammary fibroadenomas, and the presence of uterine dilatation suggest that the uterine tumors were associated with estrogen dominance in the aged female rats, which does not occur in humans.

No fertility studies in animals have been conducted with MYCAPSSA. Injectable octreotide acetate did not impair fertility in rats at doses up to 1000 mcg/kg/day, which represents 7 times the clinical dose based on octreotide injection body surface area.

14 CLINICAL STUDIES

The efficacy of MYCAPSSA was established in a 9 month, randomized, double-blind, placebo-controlled study (NCT03252353) that enrolled 56 patients with acromegaly.

In the overall study population, 54% were female and the average age of patients was 55 years. 91% of patients were Caucasian, 5% Asian, 2% Black, and 2% Other. The percentage of patients with previous pituitary surgery was 88%. The baseline IGF-1 levels (the average of 2 assessments measured within 2 weeks of randomization) was 0.80 times ULN (range: 0.5–1.1 times ULN) in the patients treated with MYCAPSSA and 0.84 times ULN (range: 0.3–1.1 times ULN) in patients treated with the placebo.

In this study, patients initiated MYCAPSSA treatment twice daily 1 month after their last injection of somatostatin analogs. The starting dose was 40 mg (20 mg in the morning and 20 mg in the evening). Dose increase was allowed during dose titration to 60 mg (40 mg in the morning and 20 mg in the evening) and to a maximal dose of 80 mg daily (40 mg in the morning and 40 mg in the evening) until patients were deemed adequately controlled based on biochemical results and/or clinical judgement. Patients then maintained their target dose until end of treatment.

The primary efficacy endpoint was somatostatin dose-adjusted proportion of patients who maintain their biochemical response, defined as an IGF-1 levels less than or equal to the ULN at the end of 9 months of treatment. 58% of patients treated with MYCAPSSA vs. 19% of patients treated with placebo maintained their biochemical response.

25% of patients treated with MYCAPSSA required discontinuation of MYCAPSSA and treatment with other somatostatin analogs at some point during the 9-month study. Criteria for somatostatin analog rescue were IGF-1 levels ≥ 1.3 times ULN and exacerbation of acromegaly signs and symptoms on two consecutive assessments while treated for at least 2 weeks with 80 mg/day or other reasons such as adverse reactions or patient's decision.

16 HOW SUPPLIED/STORAGE AND HANDLING

MYCAPSSA delayed-release 20 mg capsules are white hard gelatin capsules imprinted with "OT" on one half of the capsule and "20" on the other half.

The capsules are supplied as:

NDC Number | Package Size
10122-550-28 | Wallet of 28 capsules

Storage

Until first use, store unopened wallets of MYCAPSSA refrigerated at 2° to 8°C (36° to 46°F). Do not freeze.

After first use, opened wallets may be stored at 20° to 25°C (68° to 77°F) for up to 1 month.

17 PATIENT COUNSELING INFORMATION

Advise the patient to read the FDA-approved patient labeling (Patient Information).

Cholelithiasis and Complications of Cholelithiasis

Advise patients to contact their healthcare provider if they experience signs or symptoms of gallstones (cholelithiasis) or complications of cholelithiasis (e.g., cholecystitis, cholangitis and pancreatitis) [see Warnings and Precautions (‎5.1)].

Hypoglycemia and Hyperglycemia

Advise patients to contact their healthcare provider if they have problems with blood sugar levels, either hyperglycemia or hypoglycemia [see Warnings and Precautions (‎5.2)].

Thyroid Function Abnormalities

Inform patients that their thyroid function will be assessed periodically during treatment [see Warnings and Precautions (‎5.3)].

Cardiac Function Abnormalities

Inform patients to contact the health care provider in case they notice irregular heartbeat [see Warnings and Precautions (‎5.4)].

Steatorrhea and Malabsorption of Dietary Fats

Advise patients to contact their healthcare provider if they experience new or worsening symptoms of steatorrhea, stool discoloration, loose stools, abdominal bloating, weight loss [see Warnings and Precautions (5.5)].

Changes in Vitamin B12 Levels

Inform patients that Vitamin B12 levels may be monitored during the treatment [see Warnings and Precautions (‎5.5)].

Females and Males of Reproductive Potential

Inform female patients that treatment with MYCAPSSA may result in unintended pregnancy [see Use in Specific Populations (‎8.3)].

Rx ONLY

Manufactured by MW Encap Ltd., Scotland, UK.

Mycapssa is a registered trademark owned by the Chiesi Group. ©2024 Chiesi USA. All rights reserved.

Patient Information
MYCAPSSA® [my (as in sky)-cap-sah]
(octreotide)
delayed-release capsules, for oral use

What is MYCAPSSA?

- MYCAPSSA is an oral prescription medicine used in the long-term maintenance treatment of acromegaly in people for whom initial treatment with octreotide or lanreotide has been effective and tolerated.
- It is not known if MYCAPSSA is safe and effective in children.

Do not take MYCAPSSA if you:

- are allergic to octreotide acetate or any of the ingredients in MYCAPSSA. MYCAPSSA can cause a serious allergic reaction including anaphylactic shock. Stop taking MYCAPSSA right away and get emergency help if you have any of these symptoms:

- swelling of your tongue, throat, lips, eyes or face
- severe itching of the skin with rash or raised bumps
- chest pain

- trouble swallowing or breathing
- feeling faint
- rapid heart beat

See the end of this leaflet for a complete list of ingredients in MYCAPSSA.

Before you take MYCAPSSA, tell your healthcare provider about all of your medical conditions, including if you:

- have liver cirrhosis or liver problems
- have kidney problems
- are pregnant or plan to become pregnant. It is not known if MYCAPSSA will harm your unborn baby. MYCAPSSA may increase your chance of becoming pregnant.
- are breastfeeding or plan to breastfeed. It is not known if MYCAPSSA passes into your breast milk. Talk to your healthcare provider about the best way to feed your baby if you take MYCAPSSA.

Tell your healthcare provider about all the medicines you take, including prescription and over-the-counter medicines, vitamins, and herbal supplements.

MYCAPSSA may affect the way other medicines work, and other medicines may affect how MYCAPSSA works.

Especially tell your healthcare provider if you take oral contraceptives. Use an alternative non-hormonal method of contraception or a back-up method while taking MYCAPSSA.

Know the medicines you take. Keep a list of them to show your healthcare provider and pharmacist when you get a new medicine.

How should I take MYCAPSSA?

- Read the detailed "Instructions for Use" at the end of this Patient Information about the right way to take MYCAPSSA.
- Take MYCAPSSA exactly as your healthcare provider tells you to take it.
- Take MYCAPSSA with a glass of water on an empty stomach.
- Take MYCAPSSA at least 1 hour before a meal or at least 2 hours after a meal (for example, you could take your morning dose 1 hour before breakfast and your evening dose at bedtime).

Swallow the capsules whole. Do not crush or chew the capsules before swallowing.

What are the possible side effects of MYCAPSSA?

- gallbladder problems. MYCAPSSA may cause problems with the gallbladder. Tell your healthcare provider if you have sudden pain in your upper right stomach (abdomen), sudden pain in your right shoulder or between your shoulder blades, yellowing of your skin or the whites of your eyes, fever with chills, nausea
- blood sugar problems. MYCAPSSA may cause you to have high blood sugar (hyperglycemia), low blood sugar (hypoglycemia), or diabetes. Tell your healthcare provider if you have problems with high or low blood sugar. Your healthcare provider will check your blood sugar when you start taking MYCAPSSA or when your dose is changed.
- thyroid problems. MYCAPSSA may keep your thyroid from releasing thyroid hormones leading to hypothyroidism. Your thyroid function will be checked regularly during your treatment with MYCAPSSA.
- heart rhythm problems. Tell your healthcare provider if you have an irregular heartbeat (your heart is not beating normally).
- fatty stool. MYCAPSSA may cause your body to have issues with absorbing dietary fats. Tell your healthcare provider if you have any new or worsening symptoms including fatty stools, changes in the color of your stools, loose stools, stomach (abdominal) bloating or weight loss.
- low vitamin B12 levels in your blood. Your healthcare provider may check your vitamin B12 levels during treatment with MYCAPSSA.

The most common side effects of MYCAPSSA include:

- headache
- nausea
- diarrhea

- joint pain
- weakness
- sweating a lot

These are not all the possible side effects of MYCAPSSA. For more information, ask your healthcare provider or pharmacist.

Call your doctor for medical advice about side effects. You may report side effects to FDA at 1-800-FDA-1088.

How should I store MYCAPSSA?

- Before first use, store unopened wallets of MYCAPSSA in a refrigerator between 36°F to 46°F (2°C to 8°C).
- Do not freeze.
- After first use, store opened wallets at room temperature between 68°F to 77°F (20°C to 25°C) for up to 1 month.

Keep MYCAPSSA and all medicines out of the reach of children.

General information about the safe and effective use of MYCAPSSA.

Medicines are sometimes prescribed for purposes other than those listed in a Patient Information. Do not use MYCAPSSA for a condition for which it was not prescribed. Do not give MYCAPSSA to other people, even if they have the same symptoms you have. It may harm them.

You can ask your pharmacist or healthcare provider for information about MYCAPSSA that is written for health professionals.

What are the ingredients in MYCAPSSA?

Active ingredient: octreotide acetate

Inactive ingredients: polyvinylpyrrolidone (PVP-12), sodium caprylate, magnesium chloride, polysorbate 80, glyceryl monocaprylate, glyceryl tricaprylate, gelatin, gelatin capsules, and Acryl-EZE® (methacrylate).

Chiesi Farmaceutici S.p.A.,
Parma, Italy

For more information about MYCAPSSA call the medical information department at 1-888-661-9260 or us.medical@chiesi.com or go to www.MYCAPSSA.com and select patient information.

This Patient Information has been approved by the U.S. Food and Drug Administration.

Approved: 07/2024

INSTRUCTIONS FOR USE MYCAPSSA® [my (as in sky)-cap-sah] (octreotide) delayed-release capsules, for oral use

Read this Instructions for Use before you start taking MYCAPSSA and each time you get a refill. There may be new information. This information does not take the place of talking to your healthcare provider about your medical condition or treatment. Talk to your healthcare provider or pharmacist if you have any questions about how to use MYCAPSSA.

Important information:

- Each MYCAPSSA wallet contains twenty-eight 20-mg capsules. The number of wallets required in a 28-day period depends on your prescribed dose.

How to Use the MYCAPSSA Wallet

- Each MYCAPSSA wallet has a locking mechanism that helps to keep the medicine away from children.
- Become familiar with using the MYCAPSSA wallet so you will know how to use it the right way.

To open the wallet:

Step 1. With your left thumb, gently press the tip of the release button on the left side of the wallet (see Figure A).

Step 2. While holding the release button, grasp the medicine card at the notch on the right side and pull it out (see Figure A).

Step 3. Unfold the medicine card (see Figure A).

Figure A: How to Open the MYCAPSSA Wallet

How to Remove a Capsule from the MYCAPSSA Wallet

Capsules need to be removed carefully, because if they are cracked or broken they may not be as effective. Follow these instructions to easily remove capsules without damaging them.

- Place the tip of a thumb at the edge of a capsule's plastic cavity (see Figure B).
- Gently push the capsule until it is removed. Collect the removed capsule in your hand.
- Do not use two thumbs to push a capsule as this could damage it.
- Do not press the middle of a capsule. This could also damage it.
- If a capsule is cracked or broken, throw it away (discard it) and remove another capsule.

Figure B: How to Remove a Capsule from the Medicine Card Inside the MYCAPSSA Wallet

This Instructions for Use has been approved by the U.S. Food and Drug Administration.
Approved: 01/2024

PRINCIPAL DISPLAY PANEL - 20 mg Blister Pack

Always take with a glass of water on an empty stomach at least
1 hour before a meal or at least 2 hours after a meal.

Mycapssa®
(octreotide) delayed-release capsules

20 mg*

2

28 Capsules

*Each capsule contains octreotide 20 mg (provided as octreotide acetate).
Acetate composition varies. See prescribing information.

PRINCIPAL DISPLAY PANEL - 20 mg Blister Pack Dose Pack

NDC 10122-550-28

Mycapssa®
(octreotide) delayed-release capsules

20 mg*

Rx only

*Each capsule contains octreotide 20 mg (provided
as octreotide acetate). Acetate composition varies.
See prescribing information.
Keep out of reach of children.

1
PRESS
& HOLD
HERE

PULL OUT HERE

❶
PRESS

❷
PULL

OPENING AND CLOSING INSTRUCTIONS

- Use left thumb to push the button gently
- While holding the button down, pull out the medication card
- Press out to take capsule(s)
- Slide medication card back to lock

28 capsules

Always take with a glass of water on an empty stomach at least
1 hour before a meal or at least 2 hours after a meal.